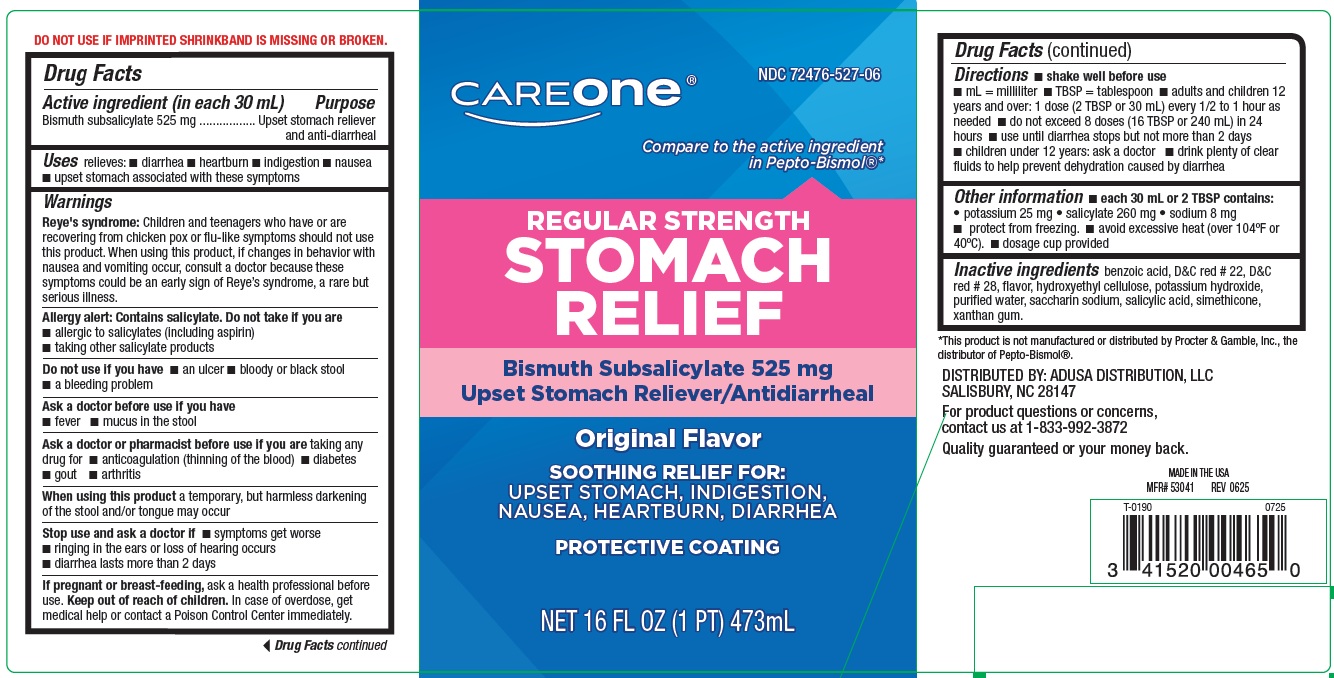 DRUG LABEL: Regular Strength Stomach Relief
NDC: 72476-527 | Form: LIQUID
Manufacturer: Retail Business Services, LLC.
Category: otc | Type: Human OTC Drug Label
Date: 20250721

ACTIVE INGREDIENTS: BISMUTH SUBSALICYLATE 525 mg/30 mL
INACTIVE INGREDIENTS: BENZOIC ACID; D&C RED NO. 22; D&C RED NO. 28; POTASSIUM HYDROXIDE; WATER; SACCHARIN SODIUM; SALICYLIC ACID; HYDROXYETHYL CELLULOSE (1500 MPA.S AT 1%); DIMETHICONE; XANTHAN GUM

Regular Strength Stomach Relief

ACTIVE INGREDIENT(in each 30 mL)

Bismuth subsalicylate 525 mg

PURPOSE

Upset stomach reliever and anti-diarrheal

USE(S)

relieves:

- diarrhea
- heartburn
- indigestion
- nausea
- upset stomach associated with these symptoms

WARNINGS

Reye's Syndrome: Children and teenagers who have or are recovering from chicken pox or flu-like symptoms should not use this product. When using this product, if changes in behavior with nausea and vomiting occur, consult a doctor because these symptoms could be an early sign of Reye's Syndrome, a rare but serious illness.
Allergy alert: Contains salicylate. Do not take if you are

- allergic to salicylates (including aspirin)
- taking other salicylate products

DO NOT USE IF YOU HAVE

- an ulcer
- bloody or black stool
- a bleeding problem

ASK A DOCTOR BEFORE USE IF YOU HAVE

- fever
- mucus in the stool

ASK A DOCTOR OR PHARMACIST BEFORE USE IF YOU ARE

taking any drug for

- anticoagulation (thinning of the blood)
- diabetes
- gout
- arthritis

WHEN USING THIS PRODUCT

a temporary, but harmless darkening of the stool and/or tongue may occur

STOP USE AND ASK DOCTOR IF

- symptoms get worse
- ringing in the ears or loss of hearing occurs
- diarrhea lasts more than 2 days

IF PREGNANT OR BREAST-FEEDING,

ask a health professional before use.

KEEP OUT OF REACH OF CHILDREN

In case of overdose, get medical help or contact a Poison Control Center immediately.

DIRECTIONS

- shake well before use
- mL = milliliter
- TBSP = tablespoon
- adults and children 12 years and over: 1 dose (2 TBSP or 30 mL) every 1/2 to 1 hour as needed
- do not exceed 8 doses (16 TBSP or 240 mL) in 24 hours
- use until diarrhea stops but not more than 2 days
- children under 12 years: ask a doctor
- drink plenty of clear fluids to help prevent dehydration caused by diarrhea

OTHER INFORMATION

- each 30 mL or 2 TBSP contains:
- potassium 25 mg
- salicylate 260 mg
- sodium 8 mg
- protect from freezing.
- avoid excessive heat (over 104oF or 40oC).
- dosage cup provided

INACTIVE INGREDIENTS

benzoic acid, D&C red # 22, D&C red # 28, flavor, hydroxyethyl cellulose, potassium hydroxide, purified water, saccharin sodium, salicylic acid, simethicone, xanthan gum.

PRINCIPAL DISPLAY PANEL

NDC 72476-527-06
compare to active ingredient in Pepto-Bismol®*

REGULAR STRENGTH STOMACH RELIEF

Bismuth Subsalicylate 525 mg
Upset Stomach Reliever/Anti-Diarrheal

Original Flavor

SOOTHING RELIEF FOR:

UPSET STOMACH, INDIGESTION,

NAUSEA, HEARTBURN, DIARRHEA

PROTECTIVE COATING

NET 16 FL OZ (1 PT) 473 mL